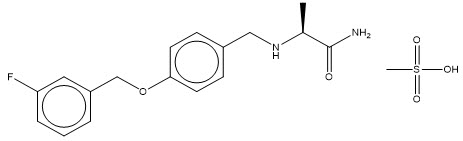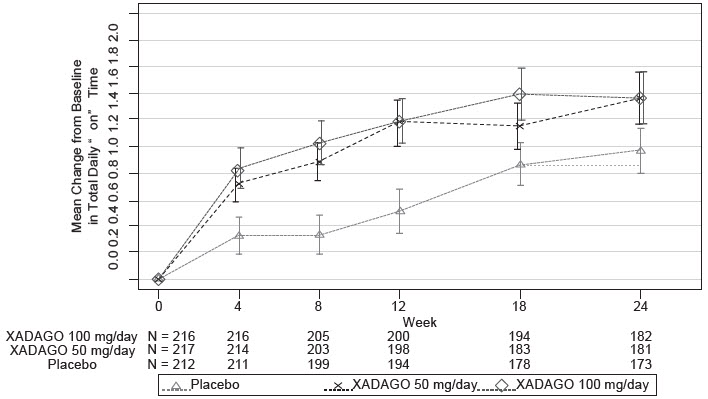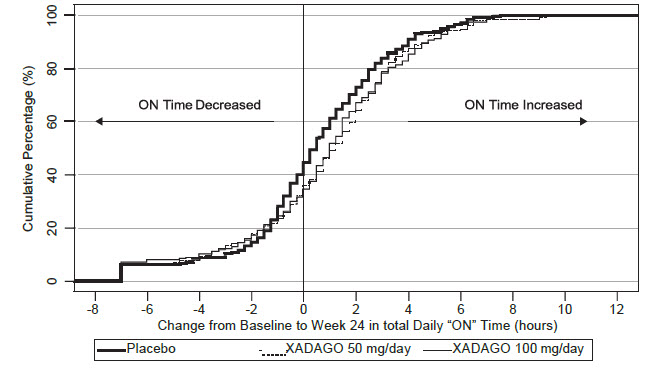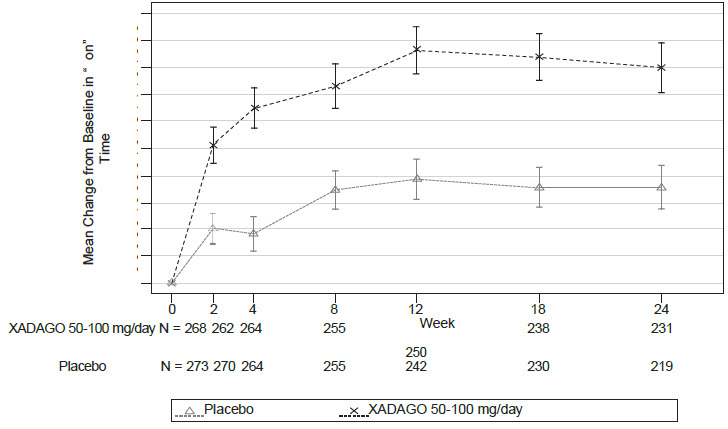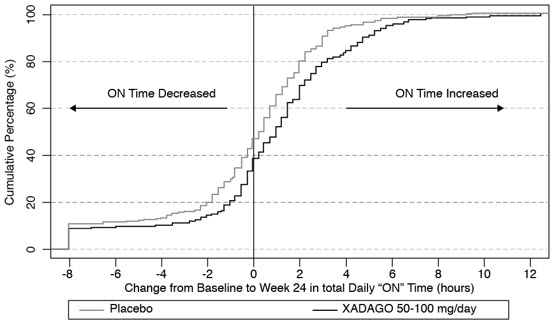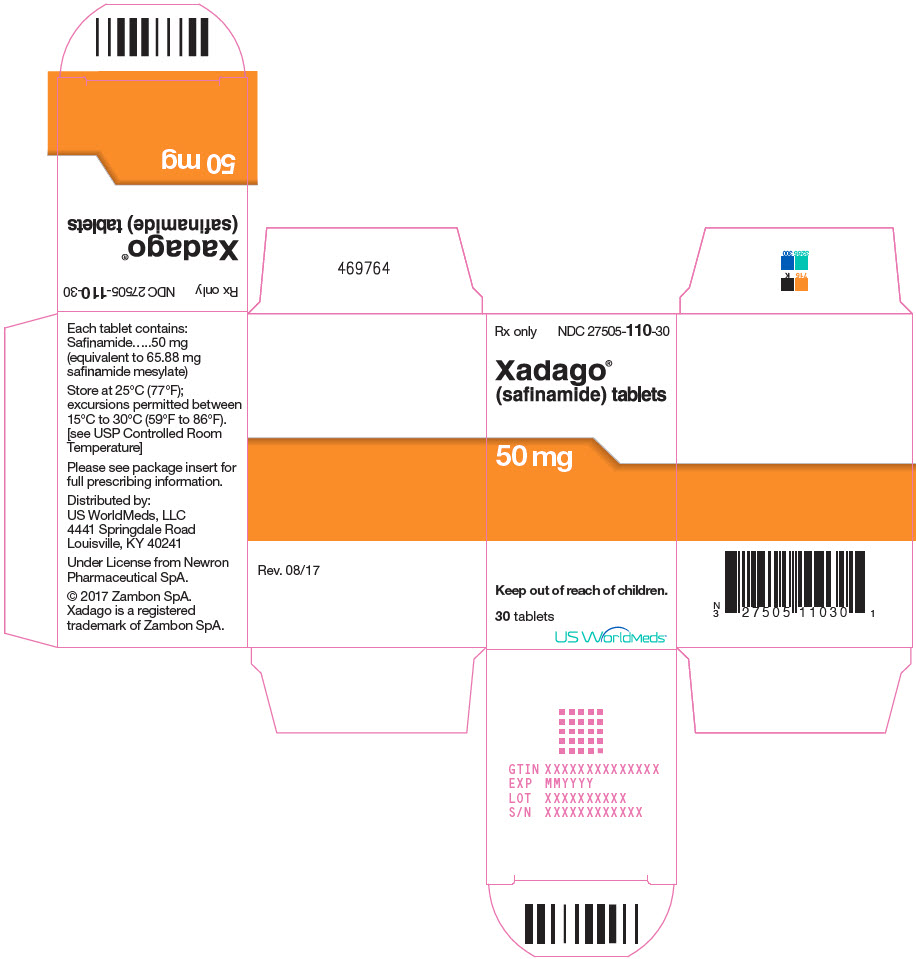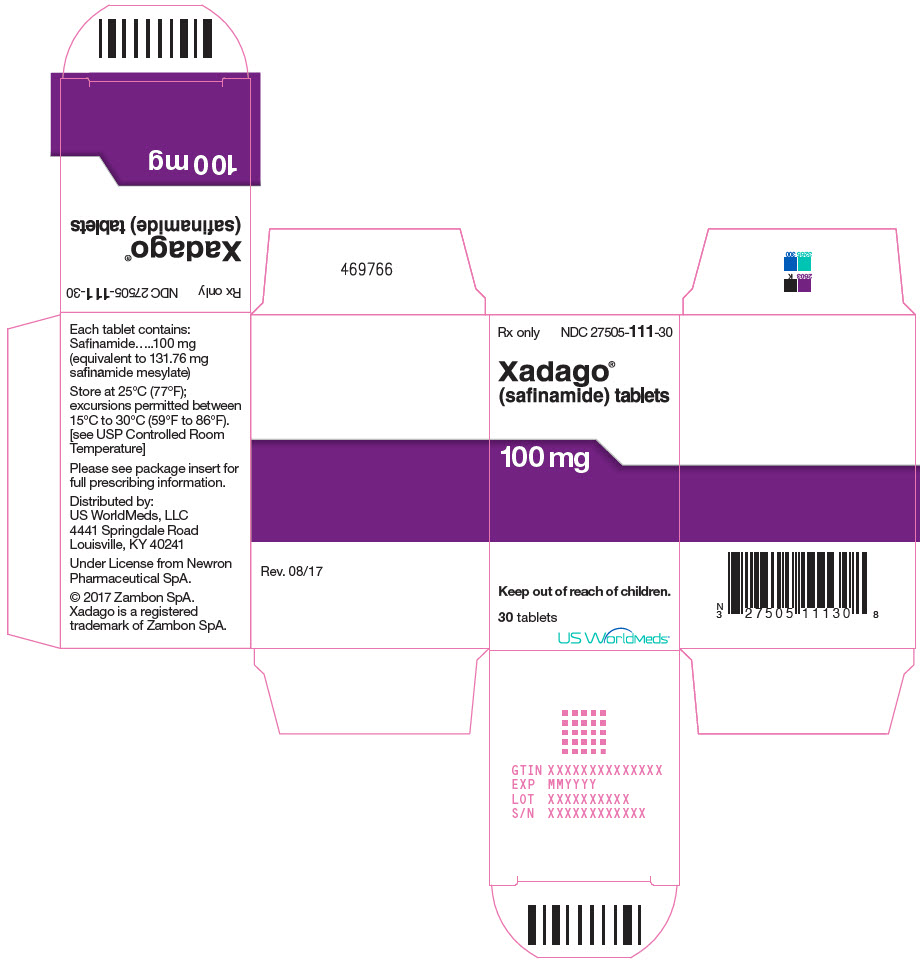 DRUG LABEL: Xadago
NDC: 27505-110 | Form: TABLET, FILM COATED
Manufacturer: MDD US Operations LLC, a subsidiary of Supernus Pharmaceuticals, Inc.
Category: prescription | Type: HUMAN PRESCRIPTION DRUG LABEL
Date: 20251022

ACTIVE INGREDIENTS: SAFINAMIDE MESYLATE 50 mg/1 1
INACTIVE INGREDIENTS: CROSPOVIDONE (120 .MU.M); MICROCRYSTALLINE CELLULOSE; MAGNESIUM STEARATE; SILICON DIOXIDE; HYPROMELLOSE, UNSPECIFIED; POLYETHYLENE GLYCOL 6000; TITANIUM DIOXIDE; FERRIC OXIDE RED; MICA

HIGHLIGHTS OF PRESCRIBING INFORMATION

These highlights do not include all the information needed to use XADAGO® safely and effectively. See full prescribing information for XADAGO®.
XADAGO® (safinamide) tablets, for oral use
Initial U.S. Approval: 2017

1 INDICATIONS AND USAGE

XADAGO is a monoamine oxidase type B (MAO-B) inhibitor indicated as adjunctive treatment to levodopa/carbidopa in patients with Parkinson's disease (PD) experiencing "off" episodes (1)

2 DOSAGE AND ADMINISTRATION

- Start with 50 mg administered orally once daily at the same time of day; after two weeks, the dose may be increased to 100 mg once daily, based on individual need and tolerability (2.1)
- Hepatic Impairment: Do not exceed 50 mg once daily in patients with moderate hepatic impairment; contraindicated in patients with severe hepatic impairment (2.2, 4)

3 DOSAGE FORMS AND STRENGTHS

Tablets: 50 mg and 100 mg (3)

4 CONTRAINDICATIONS

XADAGO is contraindicated in patients with:

- Concomitant use of the following drugs:
  - Other monoamine oxidase inhibitors or other drugs that are potent inhibitors of monoamine oxidase (e.g., linezolid) (4, 7.1)
  - Opioid drugs (e.g., tramadol, meperidine and related derivatives); serotonin-norepinephrine reuptake inhibitors; tri-or tetra-cyclic or triazolopyridine antidepressants; cyclobenzaprine; methylphenidate, amphetamine, and their derivatives; St. John's wort (4, 7.2, 7.3, 7.5)
  - Dextromethorphan (4, 7.4)
- A history of a hypersensitivity to safinamide (4)
- Severe hepatic impairment (Child-Pugh C: 10-15) (4)

5 WARNINGS AND PRECAUTIONS

- May cause or exacerbate hypertension (5.1)
- May cause serotonin syndrome when used with MAO inhibitors, antidepressants, or opioid drugs (5.2)
- May cause falling asleep during activities of daily living (5.3)
- May cause or exacerbate dyskinesia; consider levodopa dose reduction (5.4)
- May cause hallucinations and psychotic behavior (5.5)
- May cause problems with impulse control/compulsive behaviors (5.6)
- May cause withdrawal-emergent hyperpyrexia and confusion (5.7)

6 ADVERSE REACTIONS

Most common adverse reactions (incidence on XADAGO 100 mg/day at least 2% greater than placebo) were dyskinesia, fall, nausea, and insomnia (6.1)

To report SUSPECTED ADVERSE REACTIONS, contact MDD US Operations, LLC, at 1-888-492-3246 or FDA at 1-800-FDA-1088 or www.fda.gov/medwatch.

7 DRUG INTERACTIONS

- Selective Serotonin Reuptake Inhibitors: Monitor patients for serotonin syndrome (7.3)
- Sympathomimetic Medications: Monitor patients for hypertension (7.5)
- Tyramine: Risk of severe hypertension (7.6)

8 USE IN SPECIFIC POPULATIONS

Pregnancy: Based on animal data, may cause fetal harm (8.1).

FULL PRESCRIBING INFORMATION

1 INDICATIONS AND USAGE

XADAGO is indicated as adjunctive treatment to levodopa/carbidopa in patients with Parkinson's disease (PD) experiencing "off" episodes.

2 DOSAGE AND ADMINISTRATION

2.1 Dosing Information

The recommended starting dosage of XADAGO is 50 mg administered orally once daily (at the same time of day), without regard to meals. After two weeks, the dosage may be increased to 100 mg once daily, based on individual need and tolerability.

Daily dosages of XADAGO above 100 mg have not been shown to provide additional benefit, and higher dosages increase the risk for adverse reactions. XADAGO has been shown to be effective only in combination with levodopa/carbidopa [see Indications and Usage (1)] .

If a dose is missed, the next dose should be taken at the same time the next day.

XADAGO 100 mg should be tapered by decreasing the dose to 50 mg for one week before stopping [see Warnings and Precautions (5.7)] .

2.2 Dosing in Patients with Hepatic Impairment

In patients with moderate hepatic impairment (Child-Pugh B: 7-9), the maximum recommended dosage of XADAGO is 50 mg orally once daily. XADAGO is contraindicated in patients with severe hepatic impairment (Child-Pugh C: 10-15) [see Use in Specific Populations (8.6) and Clinical Pharmacology (12.3)] . If a patient taking 50 mg XADAGO progresses from moderate to severe hepatic impairment, discontinue XADAGO.

3 DOSAGE FORMS AND STRENGTHS

- 50 mg tablets: Orange to copper with metallic gloss, round, biconcave shaped embossed with "50" on one side
- 100 mg tablets: Orange to copper with metallic gloss, round, biconcave shaped embossed with "100" on one side

4 CONTRAINDICATIONS

XADAGO is contraindicated in patients with:

- Concomitant use of other drugs in the monoamine oxidase inhibitor (MAOI) class or other drugs that are potent inhibitors of monoamine oxidase, including linezolid. The combination may result in increased blood pressure, including hypertensive crisis [see Warnings and Precautions (5.1) and Drug Interactions (7.1)] .
- Concomitant use of opioid drugs (e.g., meperidine and its derivatives, methadone, propoxyphene, or tramadol); serotonin-norepinephrine reuptake inhibitors (SNRIs), tricyclic, tetracyclic, or triazolopyridine antidepressants; cyclobenzaprine; methylphenidate, amphetamine, and their derivatives; or St John's wort. Concomitant use could result in life-threatening serotonin syndrome [see Warnings and Precautions (5.2) and Drug Interactions (7.2, 7.3, 7.5)] .
- Concomitant use of dextromethorphan. The combination of MAOIs and dextromethorphan has been reported to cause episodes of psychosis or abnormal behavior [see Drug Interactions (7.4)] .
- A history of a hypersensitivity to safinamide. Reactions have included swelling of the tongue and oral mucosa, and dyspnea.
- Severe hepatic impairment (Child-Pugh C: 10-15) [see Use in Specific Populations (8.6)] .

5 WARNINGS AND PRECAUTIONS

5.1 Hypertension

XADAGO may cause hypertension or exacerbate existing hypertension. In clinical trials, the incidence of hypertension was 7% for XADAGO 50 mg, 5% for XADAGO 100 mg, and 4% for placebo. Monitor patients for new onset hypertension or hypertension that is not adequately controlled after starting XADAGO. Medication adjustment may be necessary if elevation of blood pressure is sustained.

Monitor for hypertension if XADAGO is prescribed concomitantly with sympathomimetic medications, including prescription or nonprescription nasal, oral, and ophthalmic decongestants and cold remedies [see Drug Interactions (7.5)] .

XADAGO is a selective inhibitor of MAO-B at the recommended dosages of 50 mg or 100 mg daily. Selectivity for inhibiting MAO-B decreases above the recommended daily dosages [see Clinical Pharmacology (12.2)] . Therefore, XADAGO should not be used at daily dosages exceeding those recommended because of the risks of hypertension, exacerbation of existing hypertension, or hypertensive crisis.

Dietary tyramine restriction is not required during treatment with recommended doses of XADAGO. However, use with certain foods that contain very high amounts (i.e., more than 150 mg) of tyramine could cause severe hypertension, resulting from an increased sensitivity to tyramine in patients taking recommended dosages of XADAGO, and patients should be advised to avoid such foods.

Isoniazid has some monoamine oxidase inhibiting activity. Monitor for hypertension and reaction to dietary tyramine in patients treated concomitantly with isoniazid and XADAGO [see Drug Interactions (7.1, 7.6)] .

5.2 Serotonin Syndrome

The development of a potentially life-threatening serotonin syndrome has been reported in patients on concomitant treatment with MAOIs (including selective MAO-B inhibitors), serotonin-norepinephrine reuptake inhibitors (SNRIs), tricyclic antidepressants, tetracyclic antidepressants, triazolopyridine antidepressants, cyclobenzaprine, opioid drugs (e.g., meperidine and meperidine derivatives, propoxyphene, tramadol), and methylphenidate, amphetamine, and their derivatives. Concomitant use of XADAGO with these drugs is contraindicated.

In clinical trials, serotonin syndrome was reported in a patient treated with XADAGO and a selective serotonin reuptake inhibitor (SSRI). Use the lowest effective dose of SSRIs in patients treated with concomitant XADAGO.

Serotonin syndrome symptoms may include mental status changes (e.g., agitation, hallucinations, delirium, and coma), autonomic instability (e.g., tachycardia, labile blood pressure, dizziness, diaphoresis, flushing, hyperthermia), neuromuscular symptoms (e.g., tremor, rigidity, myoclonus, hyperreflexia, incoordination), seizures, and/or gastrointestinal symptoms (e.g., nausea, vomiting, diarrhea).

5.3 Falling Asleep During Activities of Daily Living

Patients treated with dopaminergic medications have reported falling asleep while engaged in activities of daily living, including the operation of motor vehicles, which sometimes has resulted in accidents. Patients may not perceive warning signs, such as excessive drowsiness, or they may report feeling alert immediately prior to the event.

In clinical studies, sleep attacks/sudden onset of sleep were reported in patients treated with XADAGO 100 mg/day.

If a patient develops daytime sleepiness or episodes of falling asleep during activities that require full attention (e.g., driving a motor vehicle, conversations, eating), XADAGO should ordinarily be discontinued. If a decision is made to continue these patients on XADAGO, advise them to avoid driving and other potentially dangerous activities.

5.4 Dyskinesia

XADAGO may cause dyskinesia or exacerbate pre-existing dyskinesia.

In clinical trials, the incidence of dyskinesia was 21% for XADAGO 50 mg, 18% for XADAGO 100 mg, and 9% for placebo. There was a greater incidence of dyskinesia causing study discontinuation in patients treated with XADAGO 50 mg or 100 mg (1%), compared to placebo (0%) [see Adverse Reactions (6.1)] .

Reducing the patient's daily levodopa dosage or the dosage of another dopaminergic drug may mitigate dyskinesia.

5.5 Hallucinations / Psychotic Behavior

Patients with a major psychotic disorder should ordinarily not be treated with XADAGO because of the risk of exacerbating the psychosis with an increase in central dopaminergic tone. In addition, treatments for psychosis that antagonize the effects of dopaminergic medications may exacerbate the symptoms of PD [see Drug Interactions (7.7)] .

Consider dosage reduction or stopping the medication if a patient develops hallucinations or psychotic-like behaviors while taking XADAGO.

5.6 Impulse Control / Compulsive Behaviors

Patients can experience intense urges to gamble, increased sexual urges, intense urges to spend money, binge eating, and/or other intense urges, and the inability to control these urges while taking one or more of the medications, including XADAGO, that increase central dopaminergic tone. In some cases, these urges were reported to have stopped when the dose was reduced or the medication was discontinued. Because patients may not recognize these behaviors as abnormal, it is important for prescribers to specifically ask patients or their caregivers about the development of new or increased gambling urges, sexual urges, uncontrolled spending or other urges while being treated with XADAGO. Consider dose reduction or stopping the medication if a patient develops such urges while taking XADAGO.

5.7 Withdrawal Emergent Hyperpyrexia and Confusion

A symptom complex resembling neuroleptic malignant syndrome (characterized by elevated temperature, muscular rigidity, altered consciousness, and autonomic instability), with no other obvious etiology, has been reported in association with rapid dose reduction, withdrawal of, or changes in drugs that increase central dopaminergic tone.

5.8 Retinal Pathology

Retinal degeneration and loss of photoreceptor cells were observed in albino and pigmented rats administered safinamide orally in toxicity studies of up to 6 months duration. In albino rats administered safinamide orally for two years, retinal scarring and cataracts were observed at all doses tested [see Nonclinical Toxicology (13.2)] .

Periodically monitor patients for visual changes in patients with a history of retinal/macular degeneration, uveitis, inherited retinal conditions, family history of hereditary retinal disease, albinism, retinitis pigmentosa, or any active retinopathy (e.g., diabetic retinopathy).

6 ADVERSE REACTIONS

The following serious adverse reactions are discussed in greater detail in other sections of labeling:

- Hypertension [see Warnings and Precautions (5.1)]
- Serotonin Syndrome [see Warnings and Precautions (5.2)]
- Falling Asleep During Activities of Daily Living [see Warnings and Precautions (5.3)]
- Dyskinesia [see Warnings and Precautions (5.4)]
- Hallucinations / Psychotic Behavior [see Warnings and Precautions (5.5)]
- Impulse Control / Compulsive Behaviors [see Warnings and Precautions (5.6)]
- Withdrawal-Emergent Hyperpyrexia and Confusion [see Warnings and Precautions (5.7)]
- Retinal Pathology [see Warnings and Precautions (5.8)]

6.1 Clinical Trials Experience

Clinical trials are conducted under widely varying conditions; therefore, adverse reactions observed in the clinical trials of a drug cannot be directly compared to the incidence in the clinical trials of another drug and may not reflect the incidence observed in clinical practice.

Common Adverse Reactions in Placebo-Controlled PD Studies

Table 1 shows the incidence of adverse reactions with an incidence of at least 2% on XADAGO 100 mg/day and greater than placebo in controlled studies in PD (Study 1 and Study 2). The most common adverse reactions associated with XADAGO treatment in which the incidence for XADAGO 100 mg/day was at least 2% greater than the incidence for placebo were dyskinesia, fall, nausea, and insomnia.

Adverse Reactions Reported as Reason for Discontinuation from Study

In pooled placebo-controlled studies (Study 1 and Study 2) in patients with PD taking a stable dose of carbidopa/levodopa with or without other PD medications, there was an increase in the incidence of XADAGO-treated patients who discontinued from the study because of adverse reactions. The incidence of patients discontinuing from Study 1 and Study 2 for any adverse reaction was 5% for XADAGO 50 mg/day, 6% for XADAGO 100 mg/day, and 4% for placebo. The most frequently reported adverse reaction causing study discontinuation was dyskinesia (1% of patients treated with XADAGO 50 mg/day or XADAGO 100 mg/day vs. 0% for placebo).

Table 1: Percentage of Patients with Adverse Reactions with an Incidence ≥ 2% in the XADAGO 100 mg/day Group and Greater than Placebo in Studies 1 and 2.
 | XADAGO 50 mg/day (N = 223) | XADAGO 100 mg/day (N = 498) | Placebo (N = 497)
Adverse Reaction | % | % | %
Dyskinesia | 21 | 17 | 9
Fall | 4 | 6 | 4
Nausea | 3 | 6 | 4
Insomnia | 1 | 4 | 2
Orthostatic hypotension | 2 | 2 | 1
Anxiety | 2 | 2 | 1
Cough | 2 | 2 | 1
Dyspepsia | 0 | 2 | 1

Abnormal Laboratory Changes

In Study 1 and Study 2, the proportion of patients who experienced a shift from normal to above the upper limit of normal for serum alanine aminotransferase (ALT) was 5% for XADAGO 50 mg, 7% for XADAGO 100 mg, and 3% for placebo. No patient treated with XADAGO experienced an increase in ALT that was 3 times the upper limit of normal or higher.

The proportion of patients with a shift from normal to above the upper limit of normal for serum aspartate aminotransferase (AST) was 7% for XADAGO 50 mg, 6% for XADAGO 100 mg, and 3% for placebo. The incidence of patients with an increase in AST to at least 3 times the upper limit of normal was similar for XADAGO and placebo.

6.2 Postmarketing Experience

The following adverse reactions have been identified during post-approval use of safinamide. Because these reactions are reported voluntarily from a population of uncertain size, it is not always possible to reliably estimate their frequency or establish a causal relationship to drug exposure.

Immune System Disorders: Hypersensitivity: A postmarketing report describes a patient who developed a hypersensitivity reaction consisting of swelling of the tongue and gingiva, dyspnea and skin rash. The symptoms resolved shortly after XADAGO was discontinued, but reappeared following rechallenge a month later.

Nervous System Disorders: Headache

7 DRUG INTERACTIONS

7.1 MAO Inhibitors (MAOIs)

XADAGO is contraindicated for use with other drugs in the MAOIs class or other drugs that are potent inhibitors of monoamine oxidase (e.g., linezolid, an oxazolidinone antibacterial, which also has reversible nonselective MAO inhibition activity). Co-administration increases the risk of nonselective MAO inhibition, which may lead to hypertensive crisis [see Contraindications (4) and Warnings and Precautions (5.1)] . At least 14 days should elapse between discontinuation of XADAGO and initiation of treatment with other MAOIs.

Isoniazid has some monoamine oxidase inhibiting activity. Monitor for hypertension and reaction to dietary tyramine in patients treated concomitantly with isoniazid and XADAGO.

7.2 Opioid Drugs

Because serious, sometimes fatal reactions have been precipitated with concomitant use of opioid drugs (e.g., meperidine and its derivatives, methadone, propoxyphene, or tramadol) and MAOIs, including selective MAO-B inhibitors, concomitant use of these drugs is contraindicated [see Warnings and Precautions (5.2)] . At least 14 days should elapse between discontinuation of XADAGO and initiation of treatment with these drugs.

7.3 Serotonergic Drugs

Concomitant use of XADAGO with SNRIs; triazolopyridine, tricyclic or tetracyclic antidepressants; cyclobenzaprine (a skeletal muscle relaxant that is a tricyclic antidepressant derivative); or St. John's wort is contraindicated [see Warnings and Precautions (5.2)] . At least 14 days should elapse between discontinuation of XADAGO and initiation of treatment with these drugs.

Monitor patients for symptoms of serotonin syndrome if SSRIs are used by patients treated with XADAGO [see Warnings and Precautions (5.2)] .

7.4 Dextromethorphan

The combination of MAOIs and dextromethorphan has been reported to cause episodes of psychosis or bizarre behavior. Therefore, in view of XADAGO's MAO inhibitory activity, dextromethorphan is contraindicated for use with XADAGO.

7.5 Sympathomimetic Medications

Severe hypertensive reactions have followed the administration of sympathomimetics and nonselective MAOIs. Hypertensive crisis has been reported in patients taking the recommended doses of selective MAO-B inhibitors and sympathomimetic medications. Concomitant use of XADAGO with methylphenidate, amphetamine, and their derivatives is contraindicated [see Warnings and Precautions (5.1, 5.2)] .

Monitor patients for hypertension if XADAGO is prescribed concomitantly with prescription or nonprescription sympathomimetic medications, including nasal, oral, or ophthalmic decongestants and cold remedies [see Warnings and Precautions (5.1)] .

7.6 Tyramine

MAO in the gastrointestinal tract and liver (primarily type A) provides protection from exogenous amines (e.g., tyramine). If tyramine were absorbed intact, it could lead to severe hypertension, including hypertensive crisis. Aged, fermented, cured, smoked, and pickled foods containing large amounts of exogenous amines (e.g., aged cheese, pickled herring) may cause release of norepinephrine resulting in a rise in blood pressure (Tyramine Reaction). Patients should be advised to avoid foods containing a large amount of tyramine while taking recommended doses of XADAGO [see Warnings and Precautions (5.1)] .

Selectivity for inhibiting MAO-B decreases in a dose-related manner above the highest recommended daily dosage, which may increase the risk for hypertension [see Clinical Pharmacology (12.2)] . In addition, isoniazid has some monoamine oxidase inhibiting activity. Monitor for hypertension and reaction to dietary tyramine in patients treated with isoniazid and XADAGO [see Warnings and Precautions (5.1)] .

7.7 Dopaminergic Antagonists

Dopamine antagonists, such as antipsychotics or metoclopramide, may decrease the effectiveness of XADAGO and exacerbate the symptoms of PD.

8 USE IN SPECIFIC POPULATIONS

8.1 Pregnancy

Risk Summary

There are no adequate data on the developmental risk associated with the use of XADAGO in pregnant women. In animals, developmental toxicity, including teratogenic effects, was observed when safinamide was administered during pregnancy at clinically relevant doses. Developmental toxicity was observed at doses lower than those used clinically when safinamide was administered during pregnancy in combination with levodopa/carbidopa.

The background risk of major birth defects and miscarriage for the indicated population is unknown. In the U.S. general population, the estimated background risk of major birth defects and miscarriage in clinically recognized pregnancies is 2% to 4% and 15% to 20%, respectively.

Data

Animal Data

In an embryofetal development study in rats, oral administration of safinamide (0, 50, 100, or 150 mg/kg/day) throughout organogenesis resulted in dose-related increases in fetal abnormalities (primarily urogenital malformations) at all doses. A no-effect dose for adverse effects on embryofetal development was not established. The lowest dose tested (50 mg/kg/day) is approximately 5 times the maximum recommended human dose (MRHD) of 100 mg on a body surface area (mg/m^2) basis. In a combination embryofetal development study of safinamide and levodopa (LD)/carbidopa (CD) in rats (80/20 mg/kg/day LD/CD in combination with 0, 25, 50, or 100 mg/kg/day safinamide or 100 mg/kg/day safinamide alone), increased incidences of fetal visceral and skeletal malformations and variations were observed at all doses of safinamide in combination with CD/LD and with safinamide alone. The lowest dose of safinamide tested (25 mg/kg/day) is approximately 2 times the MRHD on a mg/m^2 basis.

In embryofetal development studies in rabbits, no developmental toxicity was observed at up to the highest oral dose of safinamide tested (100 mg/kg/day). However, when safinamide (0, 4, 12, or 40 mg/kg/day) was administered throughout organogenesis in a combination study of safinamide with LD/CD (80/20 mg/kg/day LD/CD), there was an increased incidence of embryofetal death and cardiac and skeletal malformations, compared to LD/CD alone. A no-effect dose for safinamide was not established; the lowest effect dose of safinamide tested (4 mg/kg/day) is less than the MRHD on a mg/m^2 basis.

In a rat pre- and postnatal development study, oral administration of safinamide (0, 4, 12.5, or 37.5 mg/kg/day) throughout pregnancy and lactation resulted in skin discoloration of the offspring, presumed to be due to hepatobiliary toxicity, at the mid and high doses and decreased body weight and increased postnatal mortality in offspring at the highest dose tested. The no-effect dose (4 mg/kg/day) for adverse developmental effects is less than the MRHD on a mg/m^2 basis.

8.2 Lactation

Risk Summary

There is no information regarding the presence of XADAGO or its metabolites in human milk, the effects on the breastfed infant, or the effects on milk production.

The developmental and health benefits of breastfeeding should be considered along with the mothers' clinical need for XADAGO and any potential adverse effects on the breastfed infant from XADAGO or from the underlying maternal condition.

Data

Animal Data

Skin discoloration, presumed to be caused by hyperbilirubinemia resulting from hepatobiliary toxicity, was observed in rat pups indirectly exposed to safinamide through the milk during the lactation period.

8.4 Pediatric Use

Safety and effectiveness in pediatric patients have not been established.

8.5 Geriatric Use

Of the 1516 subjects exposed to XADAGO in clinical studies, 38% were 65 and over, while 4% were 75 and over. No overall differences in safety or effectiveness were observed between these patients and younger patients, and other reported clinical experience has not identified differences in responses between the elderly and younger patients, but greater sensitivity of some older individuals cannot be ruled out.

8.6 Hepatic Impairment

XADAGO plasma concentrations are increased in patients with hepatic impairment [see Clinical Pharmacology (12.3)] .

In patients with moderate hepatic impairment (Child-Pugh B: 7-9), the maximum recommended dosage of XADAGO is 50 mg once daily [see Dosage and Administration (2.2)] . XADAGO has not been studied in patients with severe hepatic impairment (Child-Pugh C: 10-15), and is contraindicated in these patients. If patients progress from moderate to severe hepatic impairment, treatment with XADAGO should be stopped.

10 OVERDOSAGE

There is no human experience with XADAGO overdose.

There is no known antidote to XADAGO nor any specific treatment for XADAGO overdose. If an overdose occurs, XADAGO treatment should be discontinued and supportive treatment should be administered as clinically indicated. In cases of overdose with XADAGO, dietary tyramine restriction should be observed for several weeks.

The Poison Control Center should be called at 1-800-222-1222 for the most current treatment guidelines.

11 DESCRIPTION

XADAGO tablets contain safinamide, which is a MAO-B inhibitor, as the mesylate salt. Safinamide mesylate is (S)-2- [[4-[(3-fluorophenyl) methoxy]phenyl]methyl]aminopropanamide methanesulfonate (1:1) and its structural formula is below.

The molecular formula of safinamide mesylate is C17H19FN2O2∙CH4O3S and its molecular weight is 398.45.

Safinamide mesylate is a white to off-white crystalline powder. Safinamide mesylate is freely soluble in water, methanol and dimethyl sulfoxide. Safinamide mesylate is sparingly soluble in ethanol and is practically insoluble in ethyl acetate. In aqueous buffers that span a pH range of 1.2 to 7.5, safinamide mesylate is highly soluble at pH 1.2 and 4.5, but shows low solubility (<0.4 mg/mL) at pH 6.8 and 7.5.

XADAGO is available as 50 mg and 100 mg film-coated tablets for oral administration. Each XADAGO tablet contains 65.88 mg or 131.76 mg of safinamide mesylate, equivalent to 50 mg or 100 mg, respectively, of safinamide free base. The tablets also contain the following inactive ingredients: colloidal silicon dioxide, crospovidone, hypromellose, iron oxide (red), magnesium stearate, microcrystalline cellulose, polyethylene glycol 6000, potassium aluminum silicate, and titanium dioxide.

12 CLINICAL PHARMACOLOGY

12.1 Mechanism of Action

The precise mechanism by which XADAGO exerts its therapeutic effects in PD is unknown. XADAGO is an inhibitor of monoamine oxidase B (MAO-B). Inhibition of MAO-B activity, by blocking the catabolism of dopamine, is thought to result in an increase in dopamine levels and a subsequent increase in dopaminergic activity in the brain.

12.2 Pharmacodynamics

XADAGO inhibits monoamine oxidase B (MAO-B), with more than 1000-fold selectivity over MAO-A. In clinical studies, complete inhibition (>90%) of MAO-B was measured at doses > 20 mg.

Tyramine Challenge Test

In an oral tyramine challenge study, XADAGO produced a distinct but relatively small increase in tyramine sensitivity to increase blood pressure. The results suggest that XADAGO at a dose of 50 mg or 100 mg is relatively selective for inhibiting MAO-B and can be used without dietary tyramine restriction. Relative selectivity of XADAGO for inhibiting MAO-B decreases above the highest recommended daily dosage (100 mg) [see Warnings and Precautions (5.1) and Drug Interactions (7.6)] .

Cardiac Electrophysiology

The effect of XADAGO on the QTc interval was evaluated in a randomized placebo and positive controlled double-blind, multiple-dose parallel thorough QTc study in 240 healthy subjects. At a dose of 350 mg (3.5 times the maximum recommended dosage), XADAGO did not prolong the QTc interval.

12.3 Pharmacokinetics

Pharmacokinetics of safinamide is linear over a range of 50 mg to 300 mg (3 times the maximum recommended daily dose). Steady state is reached within 5 to 6 days.

Absorption

After single and multiple oral dosing under fasting conditions, Tmax of safinamide ranges from 2 to 3 hours. Absolute bioavailability of safinamide is 95% after oral administration, and first pass metabolism is negligible. A slight delay in Tmax was observed in the fed state relative to the fasted condition, but there was no effect on safinamide AUC0−∞ and Cmax [see Dosage and Administration (2.1)] .

Distribution

The volume of distribution (Vss) is approximately 165 L, indicating extensive extravascular distribution. Safinamide is not highly protein bound (unbound fraction is 11 to 12%).

Metabolism and Excretion

In humans, safinamide is almost exclusively eliminated via metabolism (~5% of the drug is eliminated unchanged, mainly in urine), through three main metabolic pathways. One pathway involves hydrolytic oxidation of the amide moiety leading to the primary metabolite 'safinamide acid' (NW-1153). Another pathway is oxidative cleavage of the ether bond forming 'O- debenzylated safinamide' (NW-1199). Finally, the 'N-dealkylated acid' (NW-1689) is formed by oxidative cleavage of the amine bond of either safinamide or the primary safinamide acid metabolite (NW-1153). The 'N-dealkylated acid' (NW-1689) undergoes further conjugation with glucuronic acid yielding its acyl glucuronide. NW-1689 is the main circulating metabolite in human plasma, exceeding the exposure of the parent (161% of parent). NW-1689 AG and NW-1153 account for about 18% and 11% of the parent drug exposure, respectively. None of the metabolites has pharmacological activity.

Safinamide is predominantly metabolized by non-microsomal enzymes (cytosolic amidases/MAO-A); CYP3A4 and other CYP iso-enzymes play only a minor role in its overall biotransformation.

The total clearance of safinamide was determined to be 4.6 L/h. Terminal half-life is 20-26 h. The primary route of excretion is through the kidney (76% of safinamide dose recovered in the urine, primarily in the form of inactive metabolites).

Specific Populations

Age: Geriatric Population: There are limited clinical data on the use of XADAGO in the elderly (>75 years). These data suggest that the pharmacokinetics of safinamide is not affected by age [see Use in Specific Populations (8.5)] .

Race: The pharmacokinetics of safinamide is not influenced by race.

Sex: The pharmacokinetics of safinamide is not influenced by sex.

Hepatic Impairment: The disposition of XADAGO was assessed in subjects with mild and moderate hepatic impairment and compared with subjects with normal hepatic function. A marginal increase in the exposure of safinamide (approximately 30% increase in AUC) was observed in subjects with mild hepatic impairment (Child-Pugh A). In subjects with moderate hepatic impairment (Child-Pugh B), exposure to safinamide was increased by about 80% (CI: 154-215%) [see Dosage and Administration (2.2) and Use in Specific Populations (8.6)] . XADAGO has not been studied in patients with severe hepatic impairment (Child-Pugh C) [see Contraindications (4)] .

Renal Impairment: The effect of renal impairment on safinamide pharmacokinetics was investigated in an open-label, parallel-group, single oral dose study in subjects with moderate renal impairment, severe renal impairment, or normal renal function. The pharmacokinetics of safinamide was not affected by impaired renal function.

Drug Interaction Studies

In Vitro Studies: In vitro metabolism studies indicate no meaningful inhibition or induction of Cytochrome P450 (CYP) based enzymes by safinamide and its major metabolites at concentrations that are relevant for dosing. Safinamide or its major metabolites at clinically relevant concentrations are not inhibitors of MAO-A, levodopa decarboxylase or aldehyde dehydrogenase enzymes.

Safinamide is not a substrate of P-gp. Safinamide and its metabolites did not inhibit P-gp or other transporters OCT2, OATP1B1, OATP1B3, BSEP, OAT1/3/4.

In Vivo Studies: Dedicated drug-drug interactions studies conducted with ketoconazole, levodopa (LD), BCRP substrate (rosuvastatin), and CYP1A2 and CYP3A4 substrates (caffeine and midazolam, respectively) did not demonstrate any clinically significant effects on the pharmacokinetic profile of XADAGO, or on the pharmacokinetic profile of co-administered levodopa, rosuvastatin, or CYP1A2 and CYP3A4 substrates.

13 NONCLINICAL TOXICOLOGY

13.1 Carcinogenesis, Mutagenesis, Impairment of Fertility

Carcinogenesis

In carcinogenicity studies in mice and rats, safinamide was administered at oral doses of 0, 50, 100 and 200 mg/kg/day, and 0, 25, 50 and 100 mg/kg/day, respectively, for 2 years. The highest doses tested in both species were approximately 10 times the maximum recommended human dose (MRHD) of 100 mg/day on a body surface area (mg/m^2) basis. No evidence of tumorigenic potential was observed in either species.

Mutagenesis

Safinamide was negative for genotoxicity in in vitro (Ames, mouse lymphoma) and in vivo (mouse micronucleus) assays.

Impairment of Fertility

In a rat fertility study in which males and females were orally administered safinamide (0, 50, 100, 150 mg/kg/day) prior to and during mating and continuing through early pregnancy in females, adverse effects on reproductive function were observed in both males (sperm abnormalities) and females (decreased corpora lutea, increased pre-implantation loss). The no-effect dose for reproductive toxicity (50 mg/kg/day) is approximately 5 times the MRHD on a mg/m^2 basis.

13.2 Animal Toxicology and/or Pharmacology

Retinal Pathology in Rats

Degeneration and loss of photoreceptor cells were observed in the retina of both albino and pigmented rats at plasma exposures lower than that in humans at the maximum recommended human dose of 100 mg/kg/day. The findings were dose- and time-dependent and progressed from minimal loss to severe outer nuclear cell layer loss after one year of oral dosing with safinamide. In a two year study, total retinal atrophy and scarring and lens opacities (cataracts) were seen at all oral doses tested (0, 25, 50, and 100 mg/kg/day).

In a study in rats dosed orally with safinamide alone or in combination with pramipexole, pramipexole, at a dose (25 mg/kg/day) that did not cause retinal changes, exacerbated the retinal pathology caused by safinamide alone (50 mg/kg/day) in both pigmented and albino rats.

Investigative studies were not able to identify a mechanism underlying the retinal toxicity; the relevance to humans is unknown.

14 CLINICAL STUDIES

14.1 Adjunctive Treatment in Patients with Parkinson's Disease Experiencing OFF Time on a Stable Dose of Levodopa.

Two double-blind, placebo-controlled, multi-national, 24-week studies (Study 1 and Study 2) were conducted in PD patients experiencing "OFF" Time during treatment with carbidopa/levodopa and other PD medications, e.g., dopamine agonists, catechol-O-methyl transferase (COMT) inhibitors, anticholinergics, and/or amantadine. In both studies, the primary measure of effectiveness was the change from baseline in total daily "ON" Time without troublesome dyskinesia (i.e., "ON" Time without dyskinesia plus "ON" Time with non-troublesome dyskinesia), based on 18-hour diaries completed by patients for at least 3 days before each of the scheduled visits. Secondary endpoints included "OFF" Time during the diary period and reduction in Unified PD Rating Scale (UPDRS) Part III (motor examination).

In Study 1, patients (n=645) were randomized equally to treatment with XADAGO 50 mg/day (n=217 patients), XADAGO 100 mg/day (n=216 patients), or placebo (n=212 patients), and had at least one post-baseline assessment of "ON" Time.

The percentages of patients taking stable doses of other classes of PD medications, in addition to levodopa/decarboxylase inhibitor, were: dopamine agonists (61%), COMT inhibitors (24%), anticholinergics (37%), and amantadine (14%). Use of MAOIs was prohibited. The average daily dosage of levodopa was 630 mg. The mean duration of PD was approximately 8 years.

In Study 1, XADAGO 50 mg/day and 100 mg/day significantly increased "ON" Time compared to placebo (Table 2). The increase in "ON" Time without troublesome dyskinesia was accompanied by a similar significant reduction in "OFF" Time and a reduction in Unified PD Rating Scale Part III (UPDRS III) scores assessed during "ON" Time (Table 3). Improvement in "ON" Time occurred without an increase in troublesome dyskinesia.

Table 2: Change in Mean Total Daily "ON" Time ["ON" Time = "ON" Time without dyskinesia plus "ON" Time with non-troublesome dyskinesia] in Study 1
 | N | Baseline (hours) (mean ± SD) | Change from Baseline to Endpoint (LSD [LSD: Least squares difference; a positive value indicates improvement] vs. placebo) (95% CI) [95% CI: 95% Confidence Interval] p-value
Placebo | 212 | 9.3 ± 2.2 | --
XADAGO 50 mg once daily | 217 | 9.4 ± 2.2 | 0.50 (0.03, 0.96) p=0.0356
XADAGO 100 mg once daily | 216 | 9.6 ± 2.5 | 0.53 (0.07, 1.00) p=0.0238

Table 3: Secondary Measures of Effectiveness in Study 1
 | N | Baseline (hours) (mean ± SD) | Change from Baseline to Endpoint (LSD [LSD: Least squares difference; a negative value indicates improvement] vs. placebo) (95% CI) [95% CI: 95% Confidence Interval] p-value
Change in mean daily "OFF" time
Placebo | 212 | 5.3 ± 2.1 | --
XADAGO 50 mg once daily | 217 | 5.2 ± 2.0 | -0.55 (-0.93, -0.17) p=0.0049
XADAGO 100 mg once daily | 216 | 5.2 ± 2.2 | -0.57 (-0.95, -0.19) p=0.0037
Change in UPDRS Part III (Motor subscale)
Placebo | 212 | 28.6 ± 12.0 | --
XADAGO 50 mg once daily | 217 | 27.3 ± 12.8 | -1.75 (-3.24, -0.36) p=0.0212
XADAGO 100 mg once daily | 216 | 28.4 ± 13.5 | -2.48 (-3.97, -1.00) p=0.0011

The effect of XADAGO 100 mg on "ON" Time was only slightly numerically greater than the effect of XADAGO 50 mg. In addition, the time course of improvement in total daily "ON" Time was similar between both doses (Figure 1). The time course of improvement in total daily "ON" Time showed numerically greater improvement with both XADAGO 50 mg and 100 mg compared to placebo, at all post-baseline timepoints (Figure 1).

Figure 1: Mean Change from Baseline in Total Daily "ON" Time by Week and Treatment in Study 1

Figure 2 shows the empirical cumulative distribution functions (CDF) for the change from baseline to Week 24 in total daily "ON" Time in Study 1. The cumulative percentage of patients with a change in "ON" Time was similar for the XADAGO 50 mg and 100 mg groups. The cumulative percentage of patients with an increase in "ON" Time is higher for both XADAGO 50 mg and 100 mg treated patients than for placebo patients.

Figure 2: Study 1 Empirical Cumulative Distribution Functions (CDF) for the Change from Baseline to Week 24 in Total Daily "ON" Time

Patients who dropped out of the study because of an adverse reaction, lack of efficacy, non-compliance, or withdrawal of consent were treated as treatment failures and assumed to have the smallest change from baseline among all patients. The failure rates are 6.1%, 5.6%, and 6.9% for the placebo group, XADAGO 50 mg/day group, and XADAGO 100 mg/day group, respectively.

In Study 2, patients (n=549) were randomized to treatment with XADAGO 100 mg daily (n=274 patients) or placebo (n=275 patients) for up to 24 weeks. The percentages of patients taking stable doses of other classes of PD medication, in addition to levodopa/decarboxylase inhibitor, were: dopamine agonists (74%), COMT inhibitors (18%), anticholinergics (17%), and amantadine (30%). Use of MAOIs was prohibited. The average daily dosage of levodopa was 777 mg. The mean duration of PD was approximately 9 years.

In Study 2, XADAGO was significantly better than placebo for increasing "ON"Time (Table 4). The observed increase in "ON" Time without troublesome dyskinesia was accompanied by a reduction in "OFF" Time of similar magnitude and a reduction in UPDRS III score (assessed during "ON" Time). The time course of effect was similar to that showed in the above figure for Study 1. As in Study 1, the increase in "ON" Time without troublesome dyskinesia was accompanied by a similar significant reduction in "OFF" Time and a reduction in Unified PD Rating Scale Part III (UPDRS III) scores assessed during "ON" Time (Table 5).

Table 4: Change in Mean Total Daily "ON" Time ["ON" Time = "ON" Time without dyskinesia plus "ON" Time with non-troublesome dyskinesia] in Study 2
 | N | Baseline (hours) (mean ± SD) | Change from Baseline to Endpoint (LSD [LSD: Least squares difference; a positive value indicates improvement;] vs. placebo) (95% CI) [95% CI: 95% Confidence Interval] | p-value
Placebo | 273 | 9.1 ± 2.5 | -- | --
XADAGO 100 mg once daily | 270 | 9.3 ± 2.4 | 0.99 (0.58, 1.39) | < 0.001

Table 5: Secondary Measures of Effectiveness in Study 2
 | N | Baseline (hours) (mean ± SD) | Change from Baseline to Endpoint (LSD [LSD: Least squares difference; a negative value indicates improvement] vs. placebo) (95% CI) [95% CI: 95% Confidence Interval] p-value
Change in mean daily "OFF" time
Placebo | 273 | 5.36 ± 2.00 | --
XADAGO 100 mg once daily | 270 | 5.35 ± 1.98 | -1.06 (-1.43, -0.69) <0.001
Change in UPDRS Part III (Motor subscale)
Placebo | 273 | 23.03 ± 12.75 | --
XADAGO 100 mg once daily | 270 | 22.33 ± 11.79 | -1.70 (-2.89, -0.50) 0.005

The time course of improvement in total daily "ON" Time showed numerically greater improvement with XADAGO 100 mg compared to placebo at all post-baseline timepoints (Figure 3).

Figure 3: Mean Change from Baseline in Total Daily "ON" Time by Week and Treatment in Study 2

Figure 4 shows the empirical cumulative distribution functions (CDF) for the change from baseline to Week 24 in total daily "ON" Time in Study 2. The cumulative percentage of patients with an increase in "ON" Time treated with XADAGO 50 mg to 100 mg is higher than for placebo patients.

Figure 4: Study 2 Empirical Cumulative Distribution Functions (CDF) for the Change from Baseline to Week 24 in Total Daily "ON" Time

16 HOW SUPPLIED/STORAGE AND HANDLING

16.1 How Supplied

50 mg (orange to copper colored with metallic gloss, round film-coated, biconcave shaped tablet embossed with "50" on one side; approximately 7 mm in diameter).

 | Bottles of 30 tablets | NDC 27505-110-30
 | Bottles of 90 tablets | NDC 27505-110-90

100 mg (orange to copper colored with metallic gloss, round film-coated, biconcave shaped tablet embossed with "100" on one side; approximately 9 mm in diameter).

 | Bottles of 30 tablets | NDC 27505-111-30
 | Bottles of 90 tablets | NDC 27505-111-90

16.2 Storage and Handling

Store at 25°C (77°F); excursions permitted between 15°C to 30°C (59°F to 86°F) [see USP controlled room temperature].

17 PATIENT COUNSELING INFORMATION

Advise the patient to read the FDA-approved patient labeling (Patient Information).

Hypertension

Advise patients that treatment with recommended doses of XADAGO may be associated with elevations of blood pressure or onset of hypertension. Tell patients who experience elevation of blood pressure while taking XADAGO to contact their healthcare provider.

Explain the risk of using higher than recommended daily doses of XADAGO, and provide a brief description of the tyramine associated hypertensive reaction.

Advise patients to avoid certain foods (e.g., aged cheese) containing a very large amount of tyramine while taking recommended doses of XADAGO because of the potential for large increases in blood pressure. If patients eat foods very rich in tyramine and do not feel well soon after eating, they should contact their healthcare provider [see Warnings and Precautions (5.1)] .

Serotonin Syndrome

Tell patients to inform their physician if they are taking, or plan to take, any prescription or over-the-counter drugs, especially antidepressants and over-the-counter cold medications, because there is a potential for interaction with XADAGO. Because patients should not use meperidine or certain other analgesics with XADAGO, they should contact their healthcare provider before taking new medications including antidepressants, analgesics, and prescription or nonprescription decongestants [see Contraindications (4) and Warnings and Precautions (5.2)] .

Falling Asleep During Activities of Daily Living and Somnolence

Inform patients about the potential for sedating effects associated with XADAGO and other dopaminergic medications, including somnolence and particularly to the possibility of falling asleep while engaged in activities of daily living. Because somnolence can be a frequent adverse reaction with potentially serious consequences, patients should not operate a motor vehicle or engage in other potentially dangerous activities until they have gained sufficient experience with XADAGO.

Advise patients that if increased somnolence or new episodes of falling asleep during activities of daily living (e.g., watching television, passenger in a car, etc.) are experienced at any time during treatment, they should not drive or participate in potentially dangerous activities until they have contacted their physician. Patients should not drive, operate machinery, or work at heights during treatment if they have previously experienced somnolence and/or have fallen asleep without warning prior to use of XADAGO.

Because of possible additive effects, advise patients about the potential for increased somnolence when patients are taking other sedating medications, alcohol, or other central nervous system depressants (e.g., benzodiazepines, antipsychotics, antidepressants) in combination with XADAGO [see Warnings and Precautions (5.3)] .

Dyskinesia

Advise patients taking XADAGO as adjunct to levodopa that there is a possibility of dyskinesia or increased dyskinesia [see Warnings and Precautions (5.4)] .

Hallucinations / Psychotic Behavior

Inform patients that hallucinations or other manifestations of psychotic behavior can occur when taking XADAGO. Advise patients that, if they have a major psychotic disorder, that XADAGO should not ordinarily be used because of the risk of exacerbating the psychosis. Patients with a major psychotic disorder should also be aware that many treatments for psychosis may decrease the effectiveness of XADAGO [see Warnings and Precautions (5.5) and Drug Interactions (7.7)] .

Impulse Control/Compulsive Behaviors

Advise patients that they may experience intense urges to gamble, increased sexual urges, other intense urges, and the inability to control these urges while taking XADAGO. Although it is not proven that the medications caused these events, these urges were reported to have stopped in some cases when the dose was reduced or the medication was stopped. Prescribers should ask patients about the development of new or increased gambling urges, sexual urges, or other urges while being treated with XADAGO. Patients should inform their physician if they experience these urges while taking XADAGO [see Warnings and Precautions 5.6] .

Withdrawal-Emergent Hyperpyrexia and Confusion

Tell patients to contact their healthcare provider if they wish to discontinue XADAGO and seek guidance for tapering XADAGO instead of abruptly discontinuing XADAGO [see Warnings and Precautions (5.7)] .

Missing Dose

Instruct patients to take XADAGO as prescribed. If a dose is missed, instruct patients to take the next dose at the usual time on the following day.

Concomitant Medications

Advise patients to inform their physicians if they are taking, or plan to take, any prescription or over-the-counter medications because of a potential for interactions [see Contraindications (4), and Drug Interactions (7.3, 7.4, and 7.5)] .

Distributed by:
MDD US Operations, LLC
9715 Key West Ave
Rockville, MD 20850

Under License from Newron Pharmaceuticals SpA.

MDD US Operations, LLC is the exclusive licensee and distributor of XADAGO in the United States and Its territories.

©20xx. Zambon SpA. XADAGO is a registered trademark of Zambon SpA.

298558

A_HQ_2019000185-1

PATIENT INFORMATION
XADAGO® (ZA-da-go)
(safinamide) Tablets

What is XADAGO?

XADAGO is a type of prescription medicine known as a monoamine oxidase type B (MAO-B) inhibitor used with levodopa and carbidopa to treat adults with Parkinson's disease (PD) who are having "off" episodes.

It is not known if XADAGO is safe and effective in children.

Do not take XADAGO if you:

- take another medicine called a Monoamine Oxidase Inhibitor (MAOI) because it may cause a sudden severe increase in your blood pressure (hypertensive crisis).
  - Do not take an MAOI within 14 days after you stop taking XADAGO.
  - Do not start XADAGO if you stopped taking an MAOI in the last 14 days.
- take an opioid drug, St. John's wort, serotonin-norepinephrine reuptake inhibitors (SNRIs), tricyclic antidepressants, tetracyclic antidepressants, triazolopyridine antidepressants, cyclobenzaprine, methylphenidate (or similar drugs), or amphetamine (or similar drugs) because it could be life-threatening. Ask your healthcare provider if you are not sure if you are taking any of these medicines.
  - Do not take XADAGO within 14 days after you stop taking any of these medicines.
  - Do not start taking XADAGO if you stopped taking any of these medicines in the last 14 days.
- take a medicine used to treat a cough or cold called dextromethorphan because it may cause psychosis or abnormal behavior.
- have a history of an allergic reaction to safinamide. Signs of an allergic reaction to safinamide could include swelling of your tongue, mouth or trouble breathing. Ask your healthcare provider if you are not sure if you have had an allergic reaction to safinamide in the past.
- have severe liver problems.

Before taking XADAGO, tell your healthcare provider about all of your medical conditions, including if you:

- have high or low blood pressure
- have a sleep disorder, have unexpected or unpredictable daytime sleepiness or take a medicine to help you sleep
- drink alcoholic beverages. This may increase your chances of becoming drowsy or sleepy while taking XADAGO
- have a history of abnormal movement (dyskinesia)
- have or have had a mental health problem such as schizophrenia, bipolar disorder or psychosis
- have or have had unusual urges
- have or have had problems with the retina in your eye or have a family history of problems with the retina
- are pregnant or plan to become pregnant. It is not known if XADAGO will harm your unborn baby.
- are breastfeeding or plan to breastfeed. It is not known if XADAGO passes into breast milk or if it can cause side effects in a breastfed baby. Talk to your healthcare provider about the best way to feed your baby if you take XADAGO.

Tell your healthcare provider about all the medicines that you take or plan to take, including prescription and over-the-counter medicines, vitamins, and herbal supplements.

XADAGO and other medicines may affect each other causing side effects. XADAGO may affect the way other medicines work, and other medicines may affect how XADAGO works.

Especially tell your healthcare provider if you take:

- selective serotonin reuptake inhibitors (SSRIs)
- meperidine, methadone, propoxyphene, tramadol
- metoclopramide

Ask your healthcare provider if you are not sure if you are taking any of these medicines.

Know the medicines you take. Keep a list of them to show your healthcare provider and pharmacist when you get a new medicine.

How should I take XADAGO?

- Take XADAGO exactly as your healthcare provider tells you to take it.
- Take XADAGO at the same time each day.
- Take XADAGO with or without food.
- If you miss a dose, take your next dose of XADAGO at the same time the next day.
- Your healthcare provider may need to change the dose of XADAGO until the dose is right for you.
- Do not start or stop taking XADAGO without talking to your healthcare provider first.
- If you take too much XADAGO, call the Poison Control Center at 1-800-222-1222 or go to the nearest hospital emergency room right away.

What should I avoid while taking XADAGO?

- Avoid certain foods and beverages that are high in tyramine such as aged, fermented, cured, smoked and pickled foods.
- Do not drive, operate heavy machinery, work in high places or do other dangerous activities until you know how XADAGO affects you.

What are the possible side effects of XADAGO?

XADAGO may cause serious side effects, including:

- high blood pressure (hypertension). XADAGO may raise your blood pressure or make your high blood pressure worse. Your healthcare provider will check your blood pressure while you take XADAGO.
- serotonin syndrome. A potentially life-threatening problem called serotonin syndrome can happen when medicines such as XADAGO are taken with certain other medicines. Symptoms of serotonin syndrome may include:

- agitation, hallucinations, coma, or other changes in mental status
- high or low blood pressure
- seizures

- problems controlling your movements or muscle twitching
- sweating or fever
- nausea or vomiting

- fast heartbeat
- muscle stiffness or tightness
- diarrhea

- falling asleep during normal activities. You may fall asleep while doing normal activities such as driving a car, doing physical tasks, or using hazardous machinery while taking XADAGO. You may suddenly fall asleep without being drowsy or without warning. This may result in having accidents. Your chances of falling asleep while doing normal activities while taking XADAGO are greater if you take other medicines that cause drowsiness. Tell your healthcare provider right away if this happens. Before starting XADAGO, be sure to tell your healthcare provider if you take any medicines that make you drowsy.
  - Do not drive or operate machinery until you know how XADAGO affects you.
- uncontrolled, sudden movements (dyskinesia). XADAGO may cause uncontrolled sudden movements or make such movements you already have worse or more frequent. Tell your healthcare provider if this happens. The doses of your anti-Parkinson's medicine may need to be changed.
- hallucinations and other psychosis. XADAGO can cause or worsen psychotic symptoms including hallucinations (seeing or hearing things that are not real), confusion, agitation, delusional beliefs (believing things that are not real), and disorganized thinking. If you have hallucinations or any of these other psychotic-like changes, talk with your healthcare provider.
- unusual urges. Some patients taking XADAGO get urges to behave in a way unusual for them. Examples of this are unusual urge to gamble, increased sexual urges, strong urges to spend money, binge eating and the inability to control these urges. If you notice or your family notices that you are developing any unusual behaviors, talk to your healthcare provider.
- problems with the retina in your eye (retinal changes). Tell your healthcare provider if your eyesight changes.

The most common side effects of XADAGO include uncontrolled, sudden movements (dyskinesia), falls, nausea, trouble sleeping or falling asleep (insomnia). These are not all the possible side effects of XADAGO.

Call your doctor for medical advice about side effects. You may report side effects to FDA at 1-800-FDA-1088.

How should I store XADAGO?

Store XADAGO at room temperature, about 68°F to 77°F (20°C to 25°C).

Keep XADAGO and all medicines out of the reach of children.

General information about the safe and effective use of XADAGO.

Medicines are sometimes prescribed for purposes other than those listed in a Patient Information leaflet. Do not use XADAGO for a condition for which it was not prescribed. Do not give XADAGO to other people, even if they have the same symptoms that you have. It may harm them. You can ask your pharmacist or healthcare provider for information about XADAGO that is written for health professionals.

What are the ingredients in XADAGO?

Active ingredient: safinamide mesylate

Inactive ingredients: microcrystalline cellulose, crospovidone, colloidal silicon dioxide, magnesium stearate, hypromellose, polyethylene glycol 6000, iron oxide (red), potassium aluminum silicate, and titanium dioxide

Distributed by:
MDD US Operations, LLC
9715 Key West Avenue
Rockville MD 20852
Under License from Newron Pharmaceuticals SpA.
MDD US Operations, LLC is the exclusive licensee and distributor of XADAGO in the United States and Its territories.
©2019. Zambon SpA. XADAGO is a registered trademark of Zambon SpA.
For more information, call 1-888-492-3246.

This Patient Information has been approved by the U.S. Food and Drug Administration

Revised: 8/2021

PRINCIPAL DISPLAY PANEL - 50 mg Tablet Bottle Carton

Rx only
NDC 27505- 110-30

Xadago®
(safinamide) tablets

50 mg

Keep out of reach of children.

30 tablets

US WorldMeds™

PRINCIPAL DISPLAY PANEL - 100 mg Tablet Bottle Carton

Rx only
NDC 27505- 111-30

Xadago®
(safinamide) tablets

100 mg

Keep out of reach of children.

30 tablets

US WorldMeds™